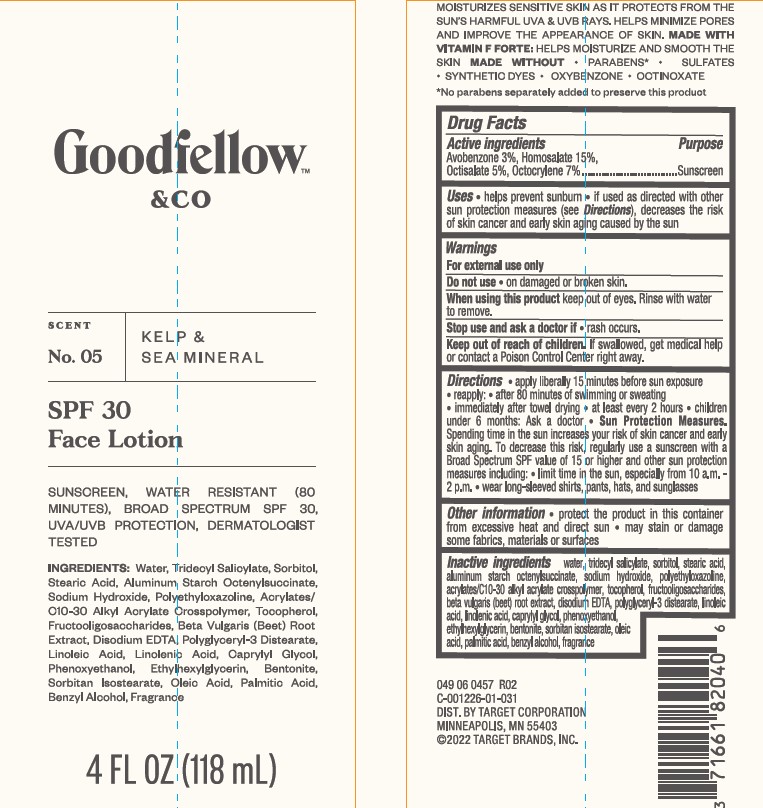 DRUG LABEL: Target Goodfellow and Co SPF 30 Face Scent No. 05 Kelp and Sea Mineral
NDC: 11673-232 | Form: LOTION
Manufacturer: TARGET CORPORATION
Category: otc | Type: HUMAN OTC DRUG LABEL
Date: 20241014

ACTIVE INGREDIENTS: AVOBENZONE 30 mg/1 mL; OCTOCRYLENE 70 mg/1 mL; OCTISALATE 50 mg/1 mL; HOMOSALATE 150 mg/1 mL
INACTIVE INGREDIENTS: TRIDECYL SALICYLATE; LINOLEIC ACID; OLEIC ACID; POLYETHYLOXAZOLINE (5000 MW); SORBITOL; .ALPHA.-TOCOPHEROL, DL-; ALUMINUM STARCH OCTENYLSUCCINATE; CAPRYLYL GLYCOL; ETHYLHEXYLGLYCERIN; STEARIC ACID; PALMITIC ACID; SORBITAN ISOSTEARATE; WATER; EDETATE DISODIUM; PHENOXYETHANOL; BENZYL ALCOHOL; BENTONITE; BETA VULGARIS ROOT FRUCTOOLIGOSACCHARIDES; BEET; POLYGLYCERYL-3 DISTEARATE; SODIUM HYDROXIDE

Target Goodfellow & Co SPF 30 Face Lotion Scent No. 05 Kelp & Sea Mineral

Active ingredients

Avobenzone 3.0%,

Homosalate 15.0%,

Octisalate 5.0%,

Octocrylene 7.0%

Purpose

Sunscreen

Uses

- helps prevent sunburn
- if used as directed with other sun protection measures (see Directions), decreases the risk of skin cancer and early skin aging caused by the sun

Warnings

For external use only

Do not use

• on damaged or broken skin.

When using this product

• keep out of eyes. Rinse with water to remove.

Stop use and ask a doctor if

• rash occurs.

Keep out of reach of children.

If swallowed, get medical help or contact a Poison Control Center right away.

Directions

- apply liberally 15 minutes before sun exposure

reapply:

- after 80 minutes of swimming or sweating
- immediately after towel drying
- at least every 2 hours
- children under 6 months of age: Ask a doctor
- Sun Protection Measures. Spending time in the sun increases your risk of skin cancer and early skin aging. To decrease this risk, regularly use a sunscreen with a Broad Spectrum SPF value of 15 or higher and other sun protection measures including:

• limit time in the sun, especially from 10 a.m. - 2 p.m.

• wear long-sleeved shirts, pants, hats, and sunglasses

Other information

- protect the product in this container from excessive heat and direct sun
- may stain or damage some fabrics, materials or surfaces

Inactive ingredients

water, TRIDECYL SALICYLATE, sorbitol, stearic acid, Aluminum Starch Octenylsuccinate, SODIUM HYDROXIDE, POLYETHYLOXAZOLINE, ACRYLATES/C10-30 ALKYL ACRYLATE CROSSPOLYMER, tocopherol, FRUCTOOLIGOSACCHARIDES, BETA VULGARIS (BEET) ROOT EXTRACT, disodium edta, polyglyceryl-3 distearate, LINOLEIC ACID, LINOLENIC ACID,CAPRYLYL GLYCOL, PHENOXYETHANOL, ETHYLHEXYLGLYCERIN, BENTONITE, Sorbitan isostearate, OILIC ACID, PALMITIC ACID BENZYL ALCOHOL, FRAGRANCE